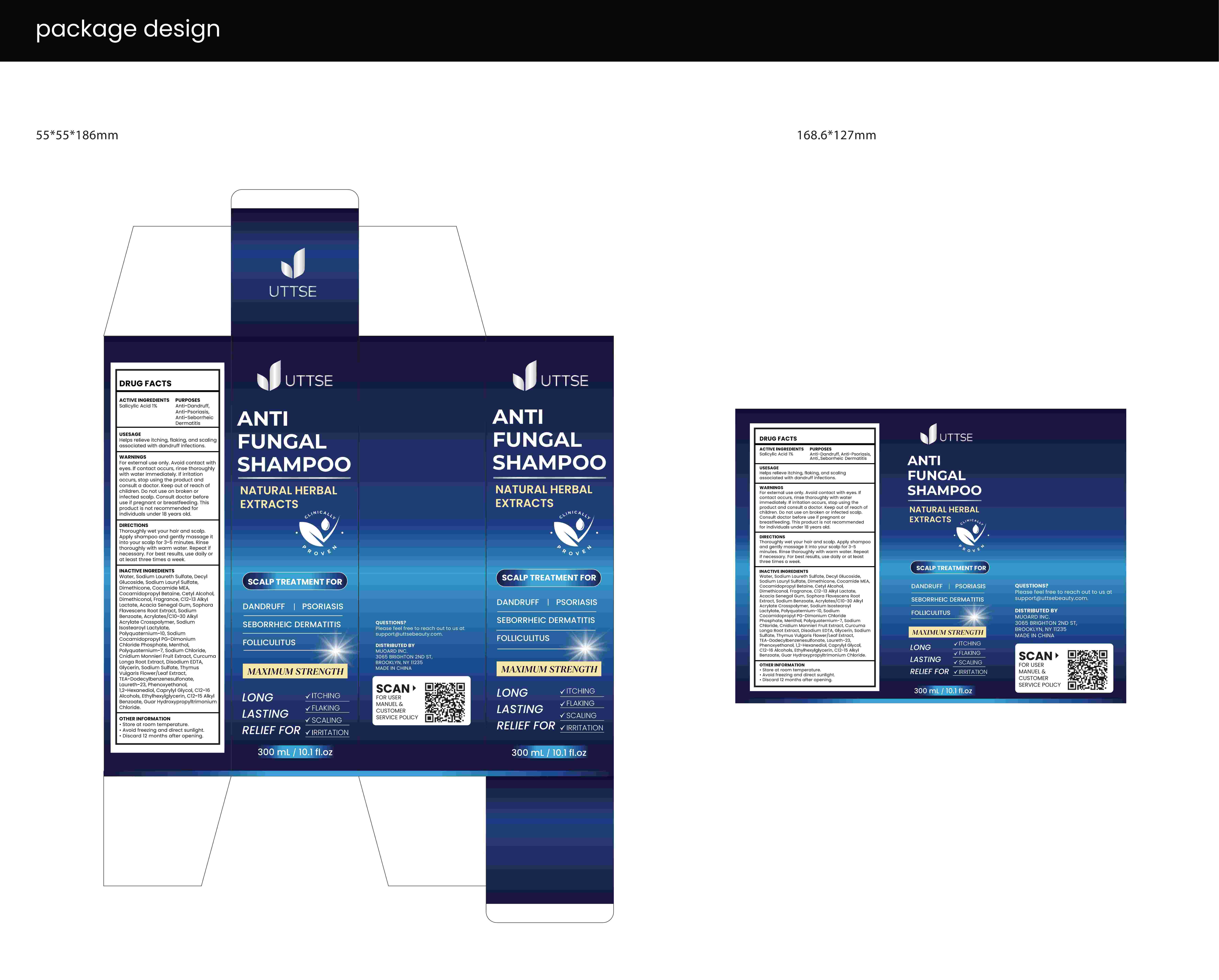 DRUG LABEL: UTTSE Anti Fungal Shampoo.
NDC: 83818-011 | Form: SHAMPOO
Manufacturer: Shenzhen Xinxin Yunhai Technology Co., Ltd.
Category: otc | Type: HUMAN OTC DRUG LABEL
Date: 20250427

ACTIVE INGREDIENTS: SALICYLIC ACID 1 g/100 mL
INACTIVE INGREDIENTS: POLYQUATERNIUM-10 (1000 MPA.S AT 2%); PHENOXYETHANOL; CAPRYLYL GLYCOL; ETHYLHEXYLGLYCERIN; C12-15 ALKYL BENZOATE; GUAR HYDROXYPROPYLTRIMONIUM CHLORIDE; SODIUM LAURETH SULFATE; SODIUM BENZOATE; FRAGRANCE 13576; COCAMIDOPROPYL BETAINE; 1,2-HEXANEDIOL; C12-16 ALCOHOLS; WATER; SOPHORA FLAVESCENS ROOT; ACRYLATES/C10-30 ALKYL ACRYLATE CROSSPOLYMER (60000 MPA.S); DIMETHICONE; POLYQUATERNIUM-7; SODIUM CHLORIDE; GLYCERIN; THYMUS VULGARIS LEAF; MENTHOL; SODIUM ISOSTEAROYL LACTYLATE; DECYL GLUCOSIDE; COCAMIDE MEA; CNIDIUM MONNIERI FRUIT; COCAMIDOPROPYL PG-DIMONIUM CHLORIDE PHOSPHATE; CURCUMA LONGA (TURMERIC) ROOT; LAURETH-23; TEA-DODECYLBENZENESULFONATE; SODIUM LAURYL SULFATE; EDETATE DISODIUM; SODIUM SULFATE; CETYL ALCOHOL; DIMETHICONOL (40 CST); C12-13 ALKYL LACTATE; ACACIA SENEGAL GUM

83818-011

Active Ingredient

Salicylic Acid 1%

Purpose

Anti-Dandruff, Anti-Psoriasis, Anti-Seborrheic Dermatitis

Use

Helps relieve itching, flaking, and scaling associated with dandruff infections.

Warnings

For external use only. Avoid contact with eyes. If contact occurs, rinse thoroughly with water immediately. If irritation occurs, stop using the product and consult a doctor. Keep out of reach of children. Do not use on broken or infected scalp. Consult doctor before use if pregnant or breastfeeding. This product is not recommended for individuals under 18 years old.

Do not use on broken or infected scalp. This product is not recommended for individuals under 18 years old.

When Using

Avoid contact with eyes. If contact occurs, rinse thoroughly with water immediately.

Stop Use

If irritation occurs, stop using the product and consult a doctor.

Ask Doctor

Consult doctor before use if pregnant or breastfeeding.

Keep Oot Of Reach Of Children

Keep out of reach of children.

Directions

Thoroughly wet your hair and scalp. Apply shampoo and gently massage it into your scalp for 3-5 minutes. Rinse thoroughly with warm water. Repeat if necessary. For best results, use daily or at least three times a week.

Other information

• Store at room temperature.
• Avoid freezing and direct sunlight.
• Discard 12 months after opening.

Inactive ingredients

Water, Sodium Laureth Sulfate, Decyl Glucoside, Sodium Lauryl Sulfate, Dimethicone, Cocamide MEA, Cocamidopropyl Betaine, Cetyl Alcohol, Dimethiconol, Fragrance, C12-13 Alkyl Lactate, Acacia Senegal Gum, Salicylic Acid, Sophora Flavescens Root Extract, Sodium Benzoate, Acrylates/C10-30 Alkyl Acrylate Crosspolymer, Sodium Isostearoyl Lactylate, Polyquaternium-10, Sodium Cocamidopropyl PG-Dimonium Chloride Phosphate, Menthol, Polyquaternium-7, Sodium Chloride, Cnidium Monnieri Fruit Extract, Curcuma Longa Root Extract, Disodium EDTA, Glycerin, Sodium Sulfate, Thymus Vulgaris Flower/Leaf Extract, TEA-Dodecylbenzenesulfonate, Laureth-23, Phenoxyethanol, 1,2-Hexanediol, Caprylyl Glycol, C12-16 Alcohols, Ethylhexylglycerin, C12-15 Alkyl Benzoate, Guar Hydroxypropyltrimonium Chloride.

Questions

Please feel free to reach out to us at support@uttsebeauty.com.